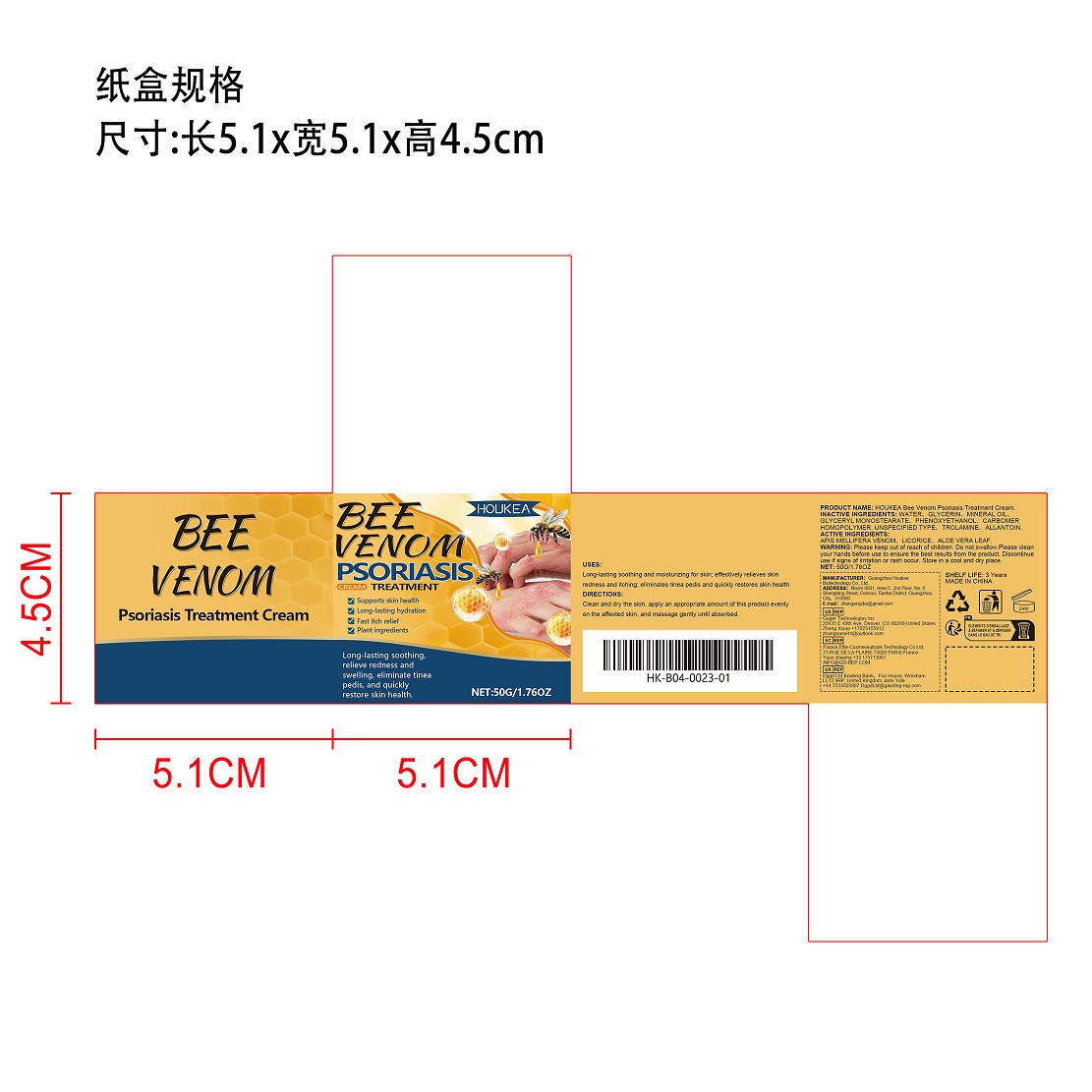 DRUG LABEL: Bee Venom Psoriasis Treatment
NDC: 84984-001 | Form: CREAM
Manufacturer: Guangzhou Houkea Biotechnology Co., Ltd.
Category: otc | Type: HUMAN OTC DRUG LABEL
Date: 20251127

ACTIVE INGREDIENTS: APIS MELLIFERA VENOM 20 g/100 g; LICORICE 7 g/100 g; ALOE VERA LEAF 3 g/100 g
INACTIVE INGREDIENTS: PHENOXYETHANOL; TROLAMINE; ALLANTOIN; CARBOMER HOMOPOLYMER, UNSPECIFIED TYPE; GLYCERYL MONOSTEARATE; WATER; GLYCERIN; MINERAL OIL

Active Ingredients

APIS MELLIFERA VENOM,LICORICE,ALOE VERA LEAF

Purpose

Supports skin health

Long-lasting hydration

Fast itch relief

use

Long-lasting soothing and moisturizing for skin; effectively relieves skin redness and itching; eliminates tinea pedis and quickly restores skin health

Warnings

Please keep out of reach of children. Do not swallow.Please cleanyour hands before use to ensure the best results from the product. Discontinueuse if sians of irritation or rash occur. Store in a cool and dry place.

DO NOT USE

NONE

WHEN USING

NONE

STOP USE

none

Please keep out of reach of children

DOSAGE AND ADMINISTRATION

Clean and dry the skin, apply an appropriate amount of this product evenlyon the affected skin, and massage gently until absorbed.

INACTIVE INGREDIENT

WATER，GLYCERIN，MINERAL OIL，GLYCERYL MONOSTEARATE，PHENOXYETHANOL，CARBOMER HOMOPOLYMER, UNSPECIFIED TYPE，TROLAMINE，ALLANTOIN